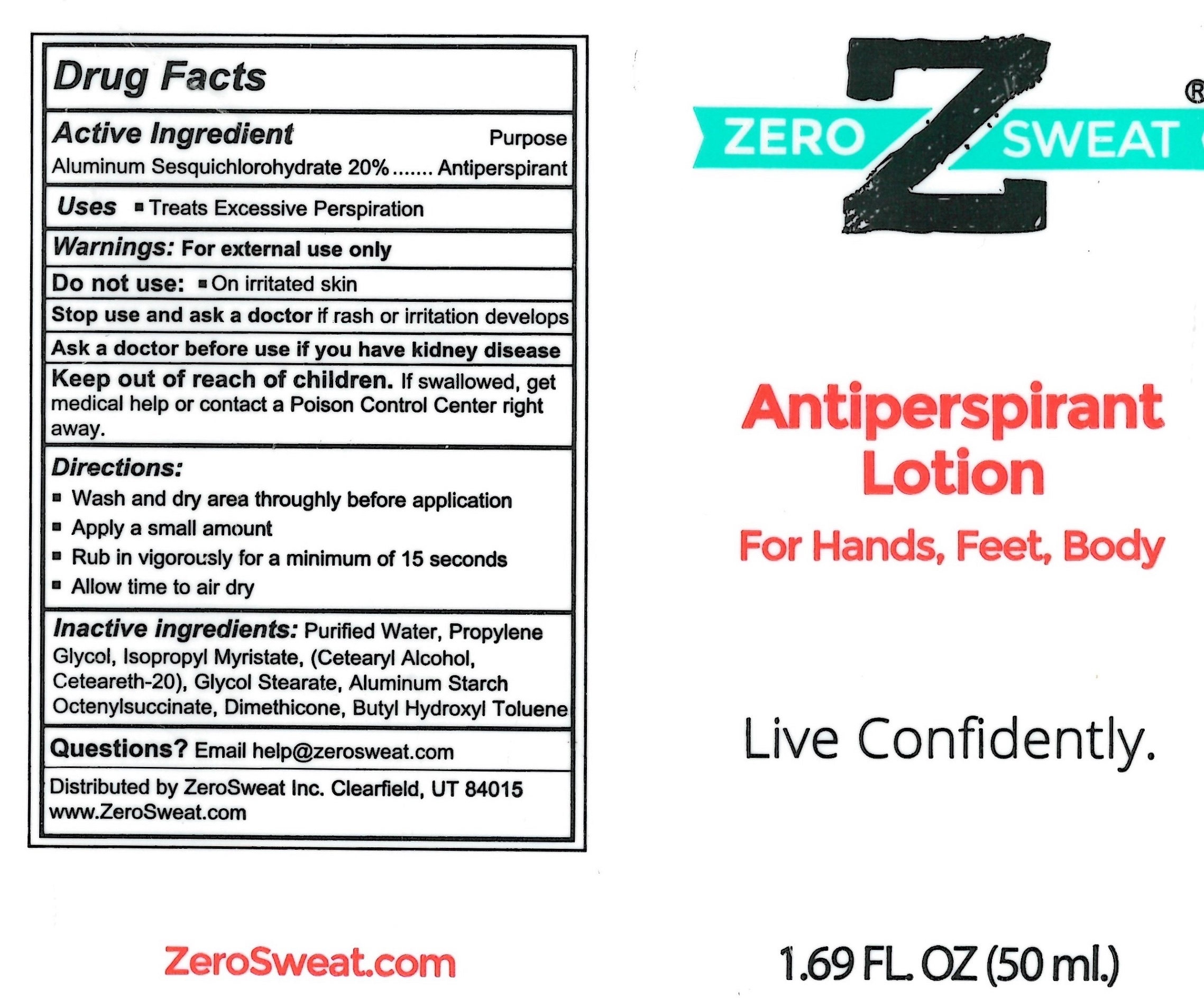 DRUG LABEL: ZeroSweat Antiperspirant For Hands Feet Body
NDC: 65112-307 | Form: LOTION
Manufacturer: I. Shay Cosmetics
Category: otc | Type: HUMAN OTC DRUG LABEL
Date: 20260130

ACTIVE INGREDIENTS: ALUMINUM SESQUICHLOROHYDRATE 0.2 g/50 mL
INACTIVE INGREDIENTS: WATER

Zero Sweat Antiperspirant Lotion 1.69oz

ACTIVE INGREDIENT

Aluminum Sesquichlorohydrate - 20%

PURPOSE

Antiperspirant

WARNING: Keep out of reach children.

INDICATIONS AND USAGE

Treats excessive perspiration

INACTIVE INGREDIENT

Purified Water, Propylene Glycol, Isopropyl Myristate, Cetearyl Alcohol, Ceteareth-20, Aluminum Starch Octenylsuccinate, Glycol Stearate, Dimethicone, Butyl Hydroxyl Toluene.

WARNINGS

For External Use Only

Do not use on irritated skin

Stop use and ask a doctor if rash or irritation develops

Keep out of reach of children.

If swallowed, get medical help or contact a Poison Control Center right away.

DOSAGE AND ADMINISTRATION

Wash and dry area thoroughly before application

Apply a small amount

Rub in vigorously for a minimum of 15 seconds

Allow time to air dry